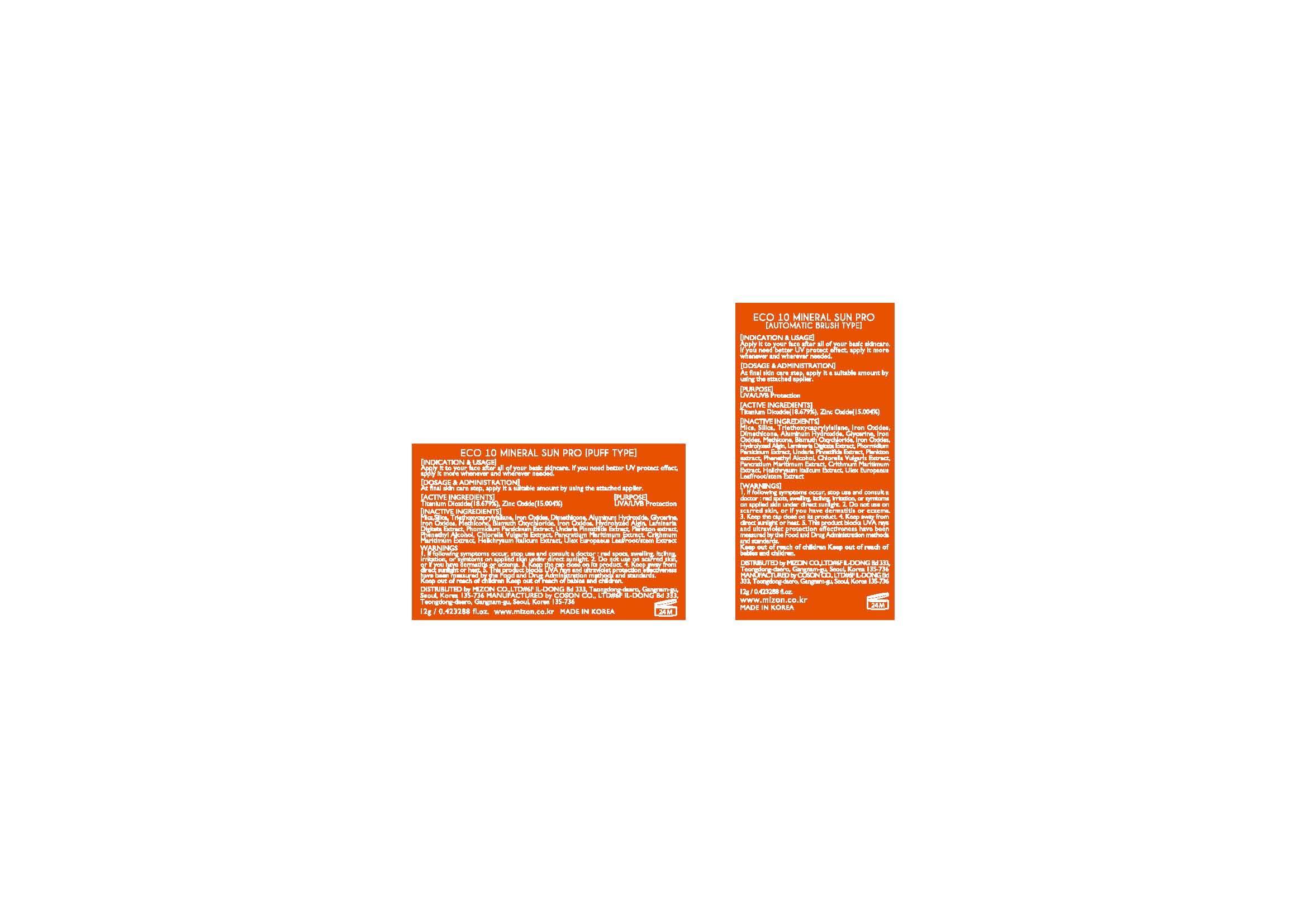 DRUG LABEL: ECO 10 Mineral Sun Pro Puff type
NDC: 57718-040 | Form: POWDER
Manufacturer: MIZON CO., LTD.
Category: otc | Type: HUMAN OTC DRUG LABEL
Date: 20140703

ACTIVE INGREDIENTS: Zinc oxide 15.004 g/100 g
INACTIVE INGREDIENTS: DIMETHICONE; ALUMINUM HYDROXIDE; HYALURONATE SODIUM; GLYCERIN; BISMUTH OXYCHLORIDE

Drug Facts

ACTIVE INGREDIENT

zinc oxide

INACTIVE INGREDIENT

Mica,Silica ,Triethoxycaprylylsilane,Iron Oxides,Dimethicone,Aluminum Hydroxide,Glycerine,
Iron Oxides,Methicone,Bismuth Oxychloride,Iron Oxides,Hydrolyzed Algin,Laminaria Digitata Extract,
Phormidium Persicinum Extract,Undaria Pinnatifida Extract ,Plankton extract,Phenethyl Alcohol ,
Chlorella vulgaris extract,Pancratium maritimum extract,Crithmum Maritimum Extract,
Helichrysum italicum extract, Ulex europaeus leaf/root/stem extract

PURPOSE

UVA/UVB protection

keep out of reach of the children

INDICATIONS AND USAGE

Apply it to your face after all of your basic skincare. If you need better UV protect effect, apply it more whenever and wherever needed

WARNINGS

1. If following symptoms occur, stop use and consult a doctor : red spots, swelling, itcihng, irritation, or symtoms on applied skin under direct sunlight.
2. Do not use on scarred skin, or if you have dermatitis or eczema
3. Keep the cap close on its product
4. Keep away from direct sunlight or heat.
5. This product blocks UVA rays and ultraviolet protection effectiveness have been measured by the Food and Drug Administration methods and standards

DOSAGE AND ADMINISTRATION

for topical use only